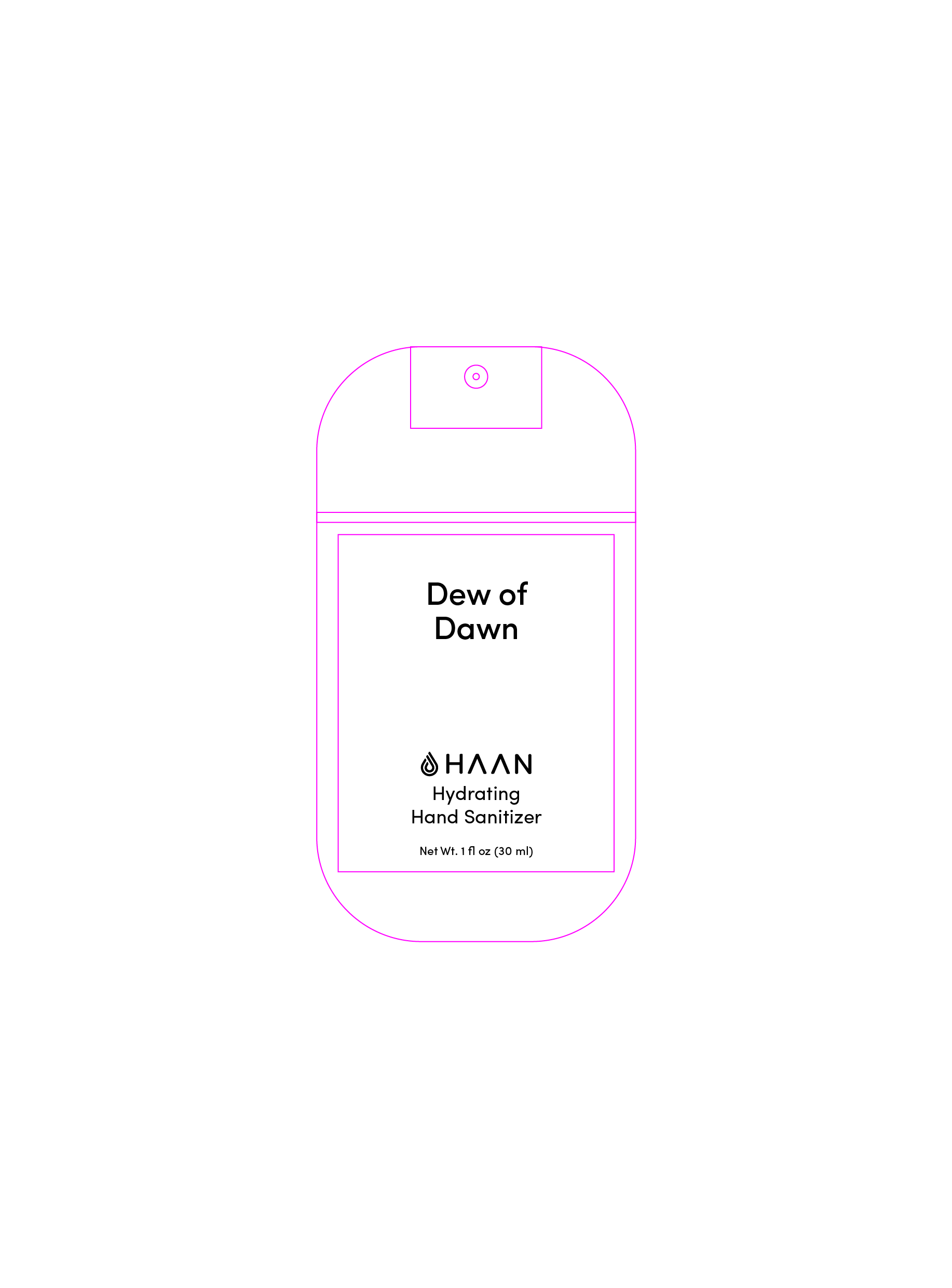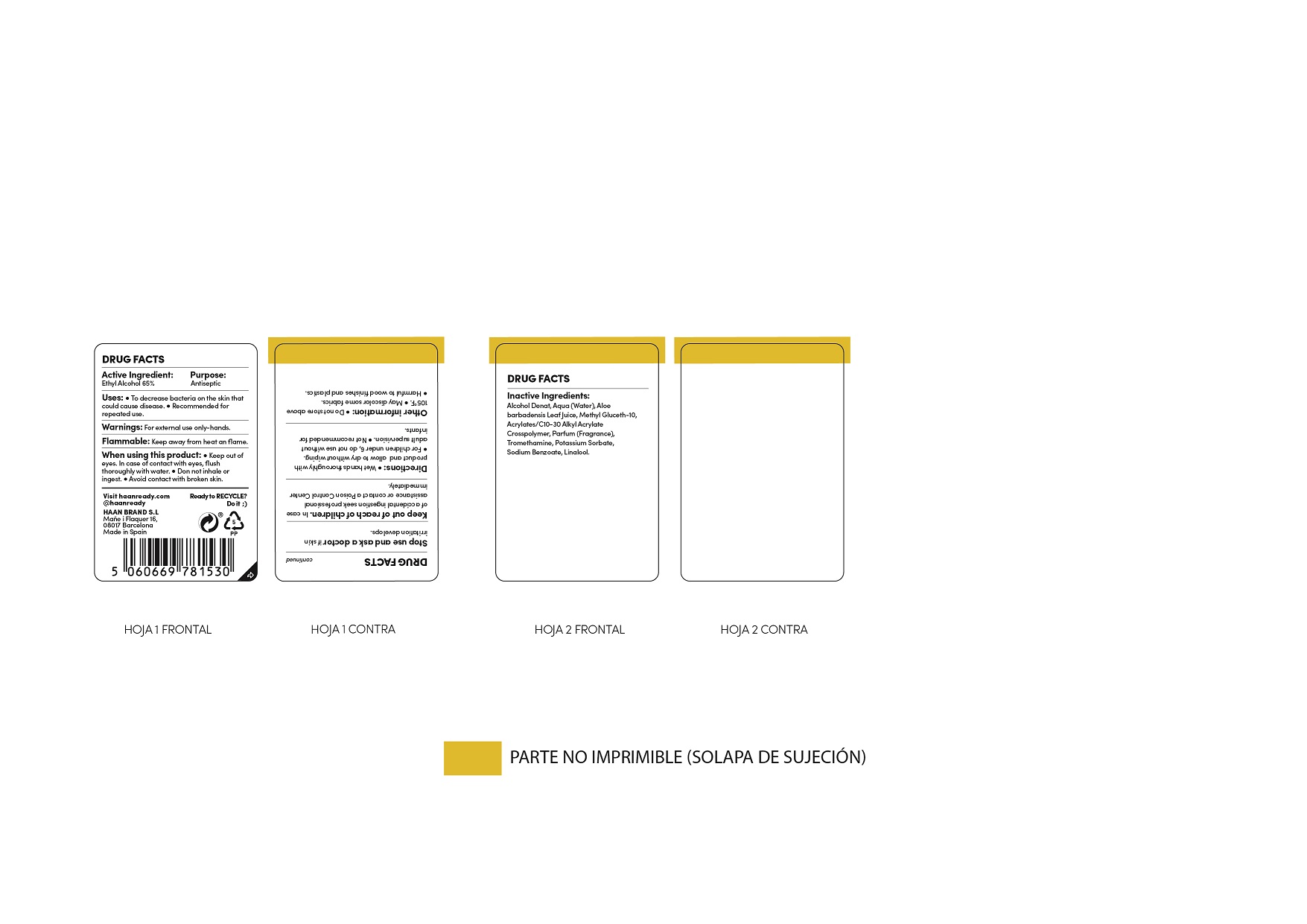 DRUG LABEL: Hand Sanitizer
NDC: 79091-008 | Form: SPRAY
Manufacturer: HAAN BRAND SL
Category: otc | Type: HUMAN OTC DRUG LABEL
Date: 20241008

ACTIVE INGREDIENTS: ALCOHOL 70 mg/1 mL
INACTIVE INGREDIENTS: SODIUM BENZOATE; CARBOMER 934; METHYL GLUCETH-10; WATER; GERANIOL; ALOE VERA LEAF; LINALOOL, (+)-; POTASSIUM SORBATE; BUTYL ACRYLATE/C16-C20 ALKYL METHACRYLATE/METHACRYLIC ACID/METHYL METHACRYLATE COPOLYMER; TROMETHAMINE

Hand Sanitizer Dew of Dawn

Uses

* To decrease bacterias on the hand. Recommended for repeated use.

Active Ingredient

Active Ingredient Purpose

- Ethyl Alcohol 65%...................................Antiseptic

Warnings

- For external use only- hands
- When using this product keep out o f eyes. In case of contact, flush throughly with water.
- Do Not Inhale or ingest.
- Avoid contact with broken skin
- Keep out of reach of children. In case of incidental ingestion seek professional assistance or contact a Poison Control Center inmediately.
- Stop use and ask Doctor: if skin irritation develops.
- Flammable: Keep away from heat and flame.

Stop use and ask a doctor if

* Irritation develops

Keep out of reach of children. In case of incidental ingestion, see professional advice or contact a Poison Control Center inmediately.

Directions

Directions: Wet hands throughly with product and allow to dry without wiping

- For Children under 6 years of age do not use without supervision of an adult. Not recomended for infants

Inactive Ingredients

Water, C10-30 Alkyl Acrylate Crosspolymer, Parfum(Fragrance), Limonene, Tromethamine, Linalool, potassium Sorbate, Geraniol, Sodium Benzoate

Questions?

QUESTIONS OR COMMENTS: Visit Haanready.com

Uses

* To decrease bacterias on the hand. Recommended for repeated use.